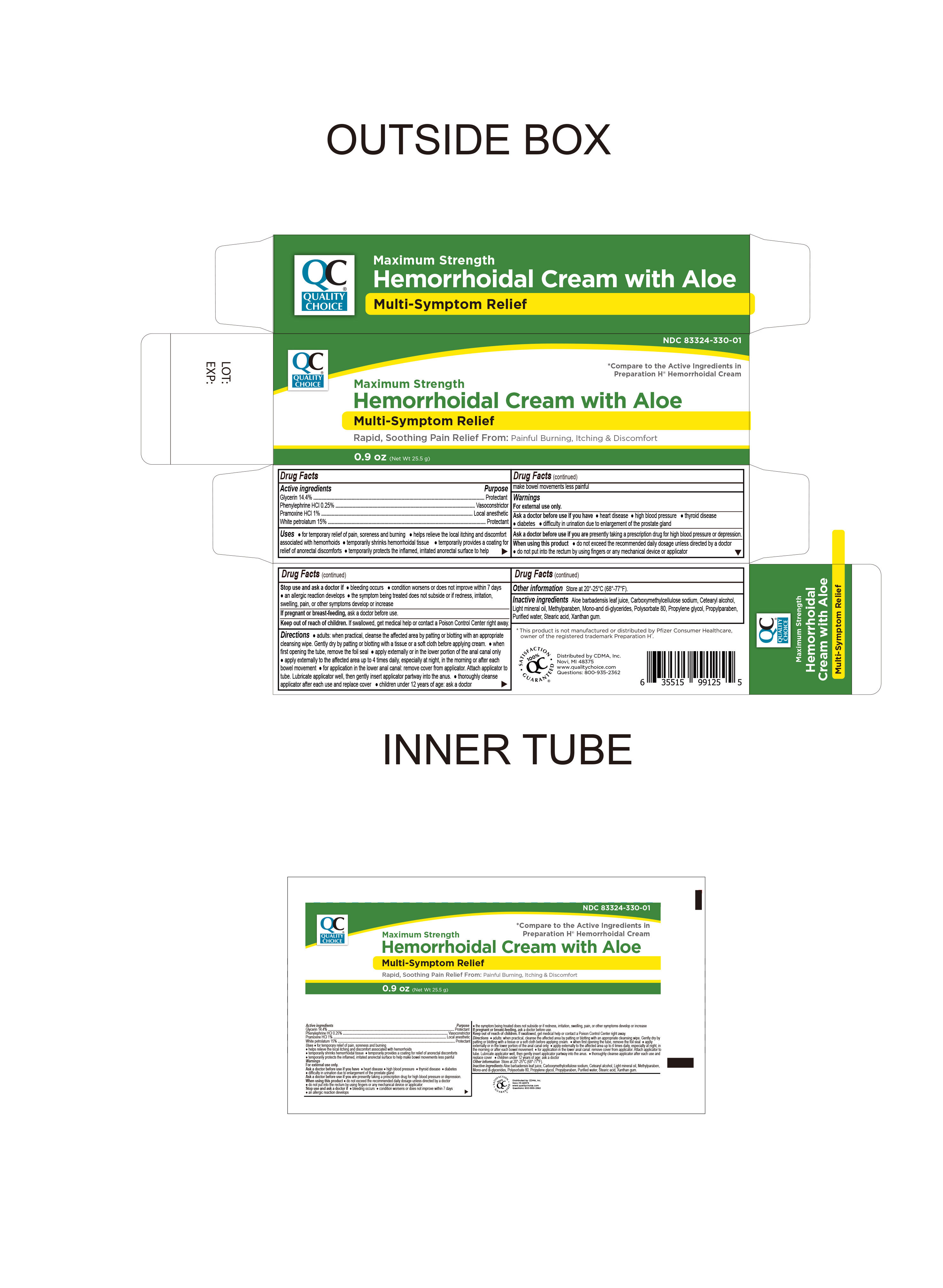 DRUG LABEL: Maximum Strength Hemorrhoidal Cream with Aloe
NDC: 83324-330 | Form: CREAM
Manufacturer: Chain Drug Marketing Association
Category: otc | Type: HUMAN OTC DRUG LABEL
Date: 20250708

ACTIVE INGREDIENTS: WHITE PETROLATUM 15 g/100 g; PHENYLEPHRINE HYDROCHLORIDE 0.25 g/100 g; PRAMOXINE HYDROCHLORIDE 1 g/100 g; GLYCERIN 14.4 g/100 g
INACTIVE INGREDIENTS: GLYCERYL MONO- AND DICAPRYLATE; CARBOXYMETHYLCELLULOSE SODIUM (0.7 CARBOXYMETHYL SUBSTITUTION PER SACCHARIDE; 100-200 MPA.S AT 1%); CETEARYL ALCOHOL; PROPYLPARABEN; LIGHT MINERAL OIL; POLYSORBATE 80; PROPYLENE GLYCOL; WATER; STEARIC ACID; XANTHAN GUM; METHYLPARABEN; ALOE VERA LEAF

Quality Choice Maximum Strength Hemorrhoidal Cream With Aloe

Active Ingredient

Glycerin 14.4%

Purpose

Protectant

Active Ingredient

Phenylephrine HCI 0.25%

Purpose

Vasoconstrictor

Active Ingredient

Pramoxine HCI 1%

Purpose

Local Anesthetic

Active Ingredient

White Petrolatum 15%

Purpose

Protectant

Uses

For temporary relief of pain, soreness and burning.

Helps relieve the local itching and discomfort associated with hemorrhoids

Temporarily shrinks hemorrhoidal tissue.

Temporarily provides a coating for relief of anorectal discomforts

Temporarily protects the inflamed, irritated anorectal surface to help make bowel movements less painful

Stop use and ask a doctor

Bleeding occurs

Condition worsens or does not improve within 7 days

An allergic reaction develops

The symptom being treated does not subside or if redness, irritation, swelling, pain or other symptoms develop or increase

If Pregnant or Breast Feeding

Ask doctor before use

Keep out of reach of children

If swallowed get medical help or contact a Poison Control Center right away

Directions

Adults:

When practical, clean the affected area by patting or blotting with an appropriate cleansing wipe. Gently dry by patting or blotting with a tissue or soft cloth before applying cream.

When first opening the tube, remove the foil seal.

Apply externally or in the lower portion of the anal canal only

Apply externally to the affected area up to 4 times daily, especially at night, in the morning or after each bowel movement

For application in the lower anal canal; remove cover from applicator. Attach applicator to tube. Lubricate applicator well, then gently insert applicator pathway into anus.

Thoroughly cleanse applicator after each use and replace cover.

Children under 12 years of age: ask a doctor

Warnings

For External Use Only

Ask doctor brfore use if you have

Heart Disease

High blood pressure

Thyroid Disease

Diabetes

Difficulty urinating due to an enlarged prostate gland

Ask doctor before use if you arepresently taking a prescription for high blood pressure or depression

When using this product

Do not exceed the recommended daily dosage unless directed by a doctor

Do not put into the rectum by using fingers or any mechanical device or applicator

Other Information

Store at room temperature 20º-25ºC (68º-77ºF)

This product is not manufactured or distributed by Pfizer Consumer Healthcare, owner of the registered trademark Preparation H®

Inactive Ingredients

Aloe barbadensis leaf juice, carboxmethylcellulose sodium, cetearyl alcohol, mono and diglycerides, methylparaben, light mineral oil, polysorbate 80, propylene glycol, propylparaben, purified water, stearic acid, xanthan gum

Questions or Comments

Call 1-800-935-2362

Distributed By

CDMA Inc.®

Novi, MI.48375, USA

800-935-2362

www.qualitychoice.com